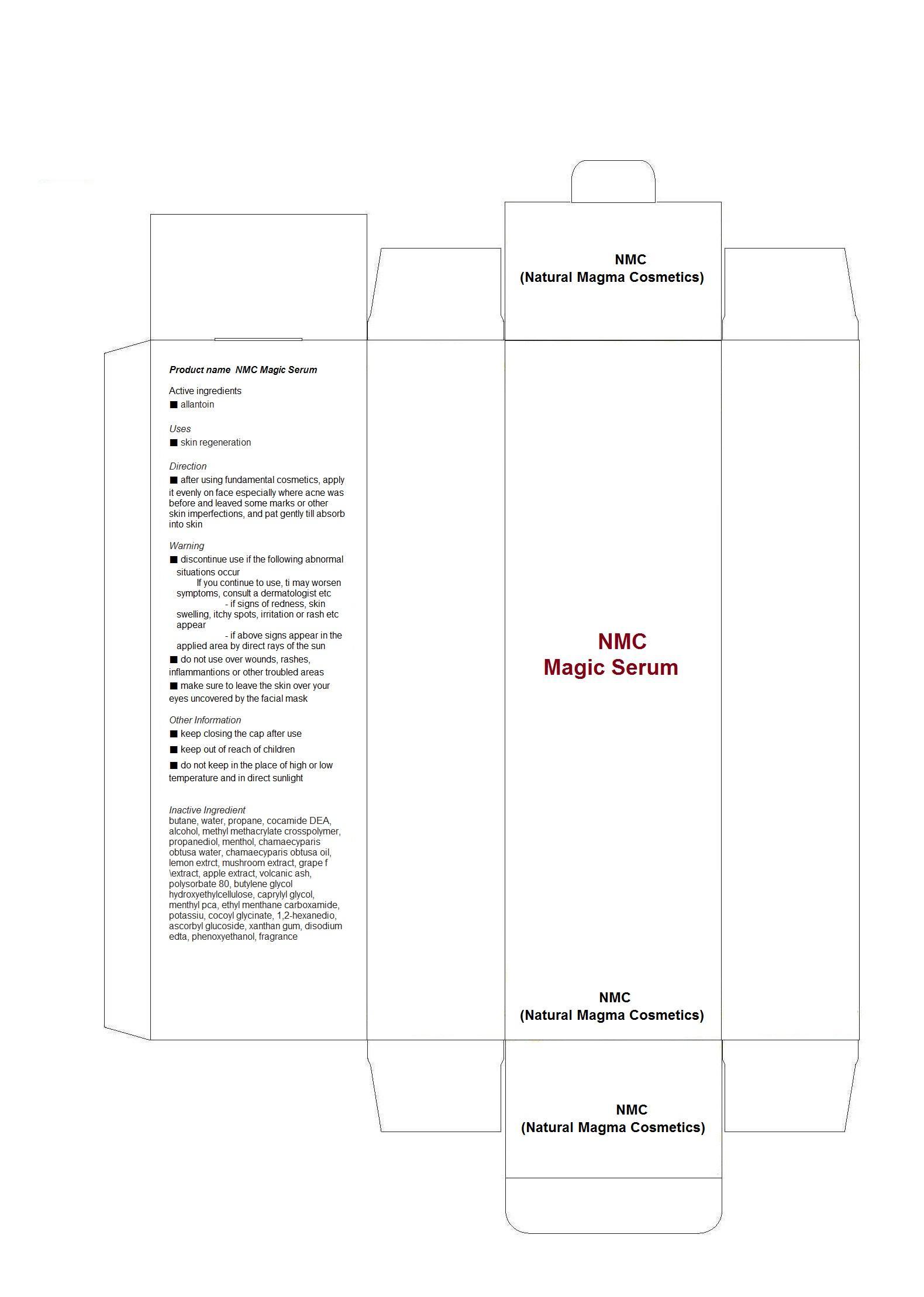 DRUG LABEL: NMC Magic Serum
NDC: 59220-2001 | Form: LIQUID
Manufacturer: NMC (Natural Magma Cosmetics)
Category: otc | Type: HUMAN OTC DRUG LABEL
Date: 20130708

ACTIVE INGREDIENTS: ALLANTOIN 1 mg/30 mL
INACTIVE INGREDIENTS: BUTANE; WATER; PROPANE; COCO DIETHANOLAMIDE; ALCOHOL; PROPANEDIOL; MENTHOL; POLYSORBATE 80; ASCORBYL GLUCOSIDE; CAPRYLYL GLYCOL; MENTHYL PYRROLIDONE CARBOXYLATE, (-),DL-; ETHYL MENTHANE CARBOXAMIDE; PHENOXYETHANOL

Drug Facts

ACTIVE INGREDIENT

allantoin

INACTIVE INGREDIENT

butane, water, propane, cocamide DEA, alcohol, methyl methacrylate crosspolymer, propanediol, menthol, chamaecyparis obtusa water, chamaecyparis obtusa oil, lemon extrct, mushroom extract, grape f\extract, apple extract, volcanic ash, polysorbate 80, butylene glycol hydroxyethylcellulose, caprylyl glycol, menthyl pca, ethyl menthane carboxamide, potassiu, cocoyl glycinate, 1,2-hexanedio, ascorbyl glucoside, xanthan gum, disodium edta, phenoxyethanol, fragrance

PURPOSE

skin regeneration

keep out or reach of the children

INDICATIONS AND USAGE

after using fundamental cosmetics, apply it evenly on face especially where acne was before and leaved some marks or other skin imperfections, and pat gently till absorb into skin

WARNINGS

■ discontinue use if the following abnormal situations occur
If you continue to use, ti may worsen symptoms, consult a dermatologist etc
- if signs of redness, skin swelling, itchy spots, irritation or rash etc appear
- if above signs appear in the applied area by direct rays of the sun
■ do not use over wounds, rashes, inflammantions or other troubled areas
■ make sure to leave the skin over your eyes uncovered by the facial mask
Other Information
■ keep closing the cap after use
■ keep out of reach of children
■ do not keep in the place of high or low temperature and in direct sunlight

DOSAGE AND ADMINISTRATION

for topical use only